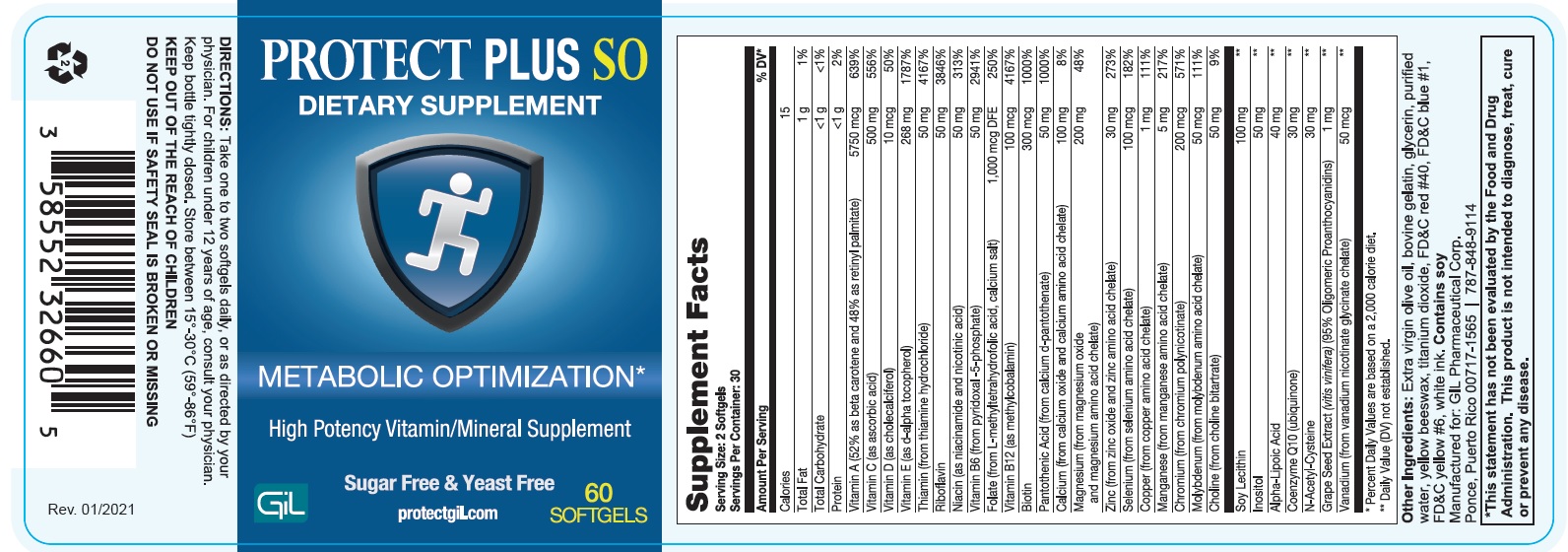 DRUG LABEL: Protect Plus SO 60
NDC: 58552-326 | Form: TABLET
Manufacturer: Gil Pharmaceutical Corp
Category: other | Type: DIETARY SUPPLEMENT
Date: 20251014

ACTIVE INGREDIENTS: VITAMIN A 5.750 mg/1 1; ASCORBIC ACID 500 mg/1 1; VITAMIN D 0.01 mg/1 1; .ALPHA.-TOCOPHEROL 268 mg/1 1; THIAMINE 50 mg/1 1; RIBOFLAVIN 50 mg/1 1; NIACIN 50 mg/1 1; PYRIDOXINE 50 mg/1 1; FOLIC ACID 1 mg/1 1; CYANOCOBALAMIN 0.1 mg/1 1; BIOTIN 0.3 mg/1 1; PANTOTHENIC ACID 50 mg/1 1; CALCIUM 100 mg/1 1; MAGNESIUM 200 mg/1 1; ZINC 30 mg/1 1; SELENIUM 0.1 mg/1 1; COPPER 1 mg/1 1; MANGANESE 5 mg/1 1; CHROMIUM 0.2 mg/1 1; MOLYBDENUM 0.05 mg/1 1; CHOLINE 50 mg/1 1; LECITHIN, SOYBEAN 100 mg/1 1; INOSITOL 50 mg/1 1; ALPHA LIPOIC ACID 40 mg/1 1; UBIDECARENONE 30 mg/1 1; ACETYLCYSTEINE 30 mg/1 1; VITIS VINIFERA SEED 1 mg/1 1; VANADIUM 0.05 mg/1 1
INACTIVE INGREDIENTS: OLIVE OIL; ALPHA-LACTALBUMIN (BOVINE); GLYCERIN; WATER; YELLOW WAX; TITANIUM DIOXIDE; FD&C RED NO. 40; FD&C BLUE NO. 1; FD&C YELLOW NO. 6

PROTECT PLUS SO
DIATERY SUPPLIMENT
METABOLIC OPTIMIZATION*
High Potency Vitamin/Mineral Supplement
Sugar Free & Yeast Free

HEALTH CLAIM

Supplement Facts
Serving Size: 2 Softgels
Servings Per Container: 30

Amount Per Serving |  | % DV*
Calories | 15
Total Fat | 1g | 1%
Total Carbohydrate | <1g | <1%
Protein | <1g | 2%
Vitamin A (52% as beta carotene and 48% as retinyl palmitate) | 5750 mcg | 639%
Vitamin C (ascorbic acid) | 500 mg | 556%
Vitamin D (as cholecalciferol) | 10 mcg | 50%
Vitamin E (as d-alpha tocopherol) | 268 mg | 1787%
Thiamin (from thiamine hydrochloride) | 50 mg | 4167%
Riboflavin | 50 mg | 3846%
Niacin (as niacinamide and nicotinic acid) | 50 mg | 313%
Vitamin B6 (from pyridoxal -5-phosphate) | 50 mg | 2941%
Folate (from L-methyltetrahydrofolic acid, calcium salt) | 1,000 mcg DFE | 250%
Vitamin B12 (as methylcobalamin) | 100mcg | 4167%
Biotin | 300 mcg | 1000%
Pantothenic Acid (from calcium d-pantothenate) | 50 mg | 1000%
Calcium (from calcium oxide and calcium amino acid chelate) | 100mg | 8%
Magnesium (from magnesium oxide and magnesium amino acid chelate) | 200 mg | 48%
Zinc (from zinc oxide and zinc amino acid chelate) | 30 mg | 273%
Selenium (from selenium amino acid chelate) | 100 mcg | 182%
Copper (from copper amino acid chelate) | 1 mg | 111%
Manganese (from manganese amino acid chelate) | 5 mg | 217%
Chromium (from chromium polynicotinate) | 200 mcg | 571%
Molybdenum (from molybdenum amino acid chelate) | 50 mcg | 111%
Choline (from choline bitartrate) | 50 mg | 9%
Soy Lecithin | 100 mg | **
Inositol | 50 mg | **
Alpha-Lipoic Acid | 40 mg | **
Coenzyme Q10 (ubiquinone) | 30 mg | **
N-Acetyl-Cysteine | 30 mg | **
Grape Seed Extract (vitis vinifera) (95% Oligomeric Proanthocyanidins) | 1 mg | **
Vanadium (from vanadium nicotinate glycinate chelate) | 50 mcg | **

* Percent Daily Values are based on a 2,000 calorie diet.
**Daily Value (DV) not established.

WARNINGS

Other Ingredients: Extra virgin olive oil, bovine gelatin, glycerin, purified water, yellow beeswax, titanium dioxide,

FD&C red #40, FD&C blue #1,FD&C yellow #6, white ink. Contains soy

STATEMENT OF IDENTITY

*This statement has not been evaluated by the Food and Drug Administration. This product is not intended to diagnose, treat, cure or prevent any disease.

DIRECTIONS:
Take one to two softgels daily, or as directed by your physician. For children under 12 years of age, consult your physician. Keep bottle tightly closed. Store between 15°-30°C (59°-86°F)

KEEP OUT OF THE REACH OF THE CHOLDREN

DO NOT USE IF SAFETY SEAL IS BROKEN OR MISSING

Manufactured for: GIL Pharmaceutical Corp.
Ponce, Puerto Rico 00717-1565 | 787-848-9114
Rev. 01/2021

PACKAGE LABEL.PRINCIPAL DISPLAY PANEL

PROTECTPLUS SO - NDC-58552-326 -60s Bottle Label